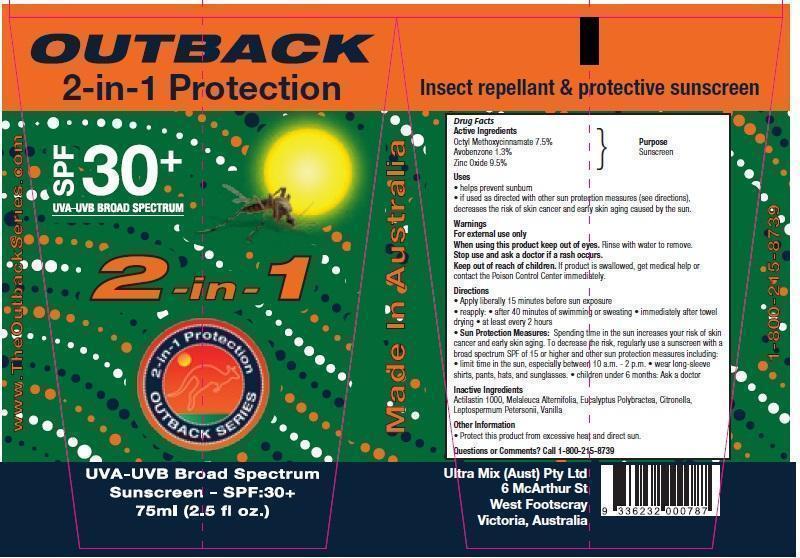 DRUG LABEL: Outback 2 in 1 Protection
NDC: 69594-005 | Form: CREAM
Manufacturer: Ultra Mix (Aust) Pty Ltd 
Category: otc | Type: HUMAN OTC DRUG LABEL
Date: 20150216

ACTIVE INGREDIENTS: OCTINOXATE 75 mg/1 mL; AVOBENZONE 13 mg/1 mL; ZINC OXIDE 95 mg/1 mL
INACTIVE INGREDIENTS: TEA TREE OIL; EUCALYPTUS POLYBRACTEA LEAF OIL; CITRONELLA OIL; LEPTOSPERMUM PETERSONII LEAF OIL

Outback 2 in 1 Protection

Active Ingredients

OCTINOXATE : 7.5 % AVOBENZONE : 1.3% ZINC OXIDE :9.5%

Inactives

TEA TREE OIL

EUCALYPTUS POLYBRACTEA LEAF OIL

CITRONELLA OIL

LEPTOSPERMUM PETERSONII LEAF OIL

VANILLA

ACTILASTIN 1000

Purpose

Sunscreen, helps prevent sunburn.

Directions of Usage

Apply liberally 15 minutes before sun exposure, reapply after 40 minutes of swimming or sweating immediately after towel drying at least every 2 hours.

Warnings

For external use only.

When using this product keep out of eyes. Rinse with water to remove. Stop use and ask a doctor if a rash occurs. Keep out of reach of children. If product is swallowed, get medical help or contact the Poison Control Center immediately.

Sun Protection Measures. Spending time in the sun increases your risk of skin cancer and early skin aging. To decrease the risk, regularly use a sunscreen with a broad spectrum SPF of 15 or higher and other sun protection measures including: limit time in the sun, especially between 10 a.m – 2 p.m. wear long-sleeve shirts, pants, hats and sunglasses. Children under 6 months: Ask a doctor